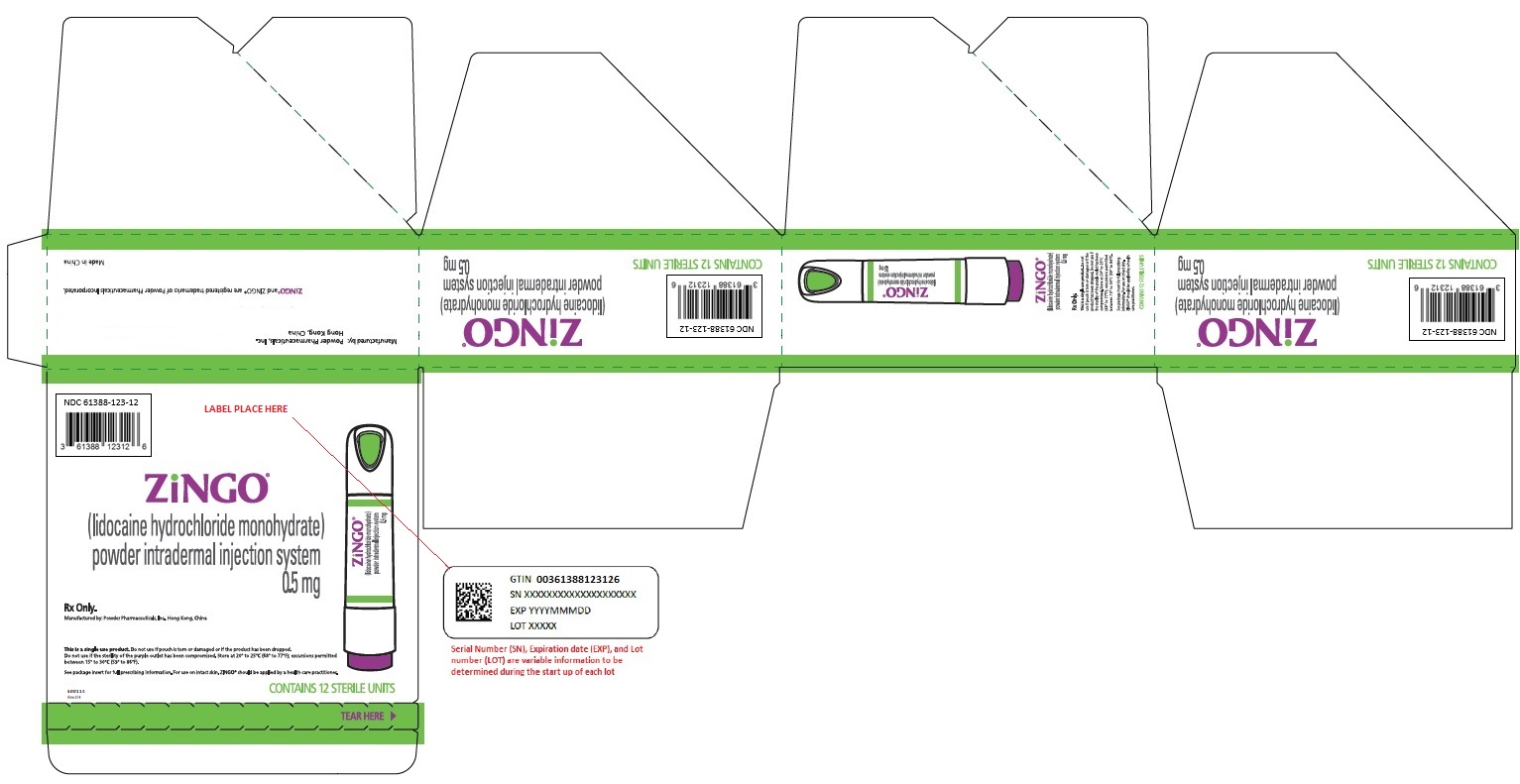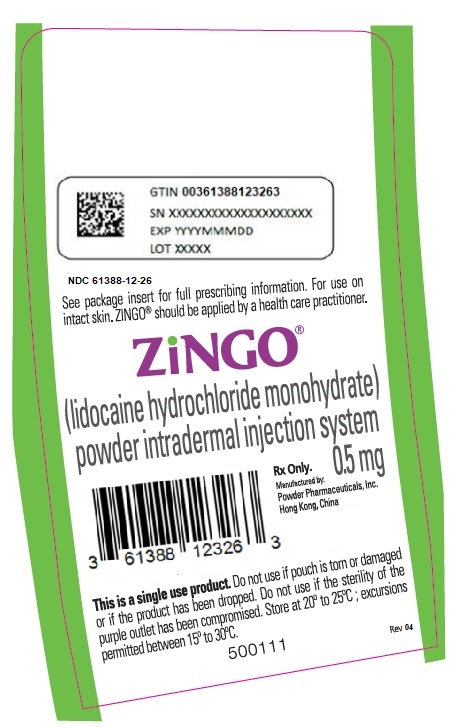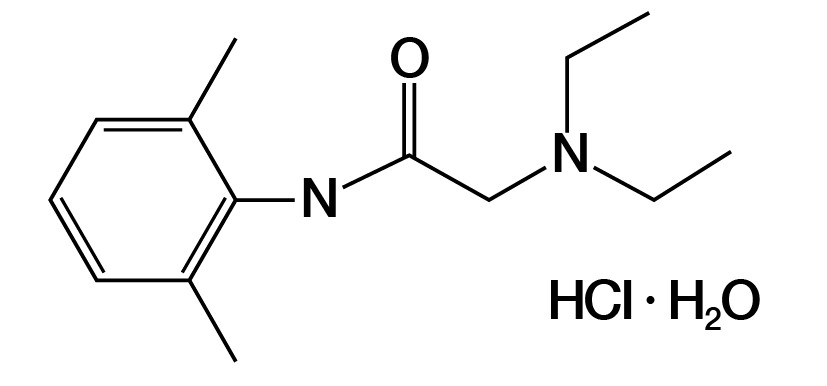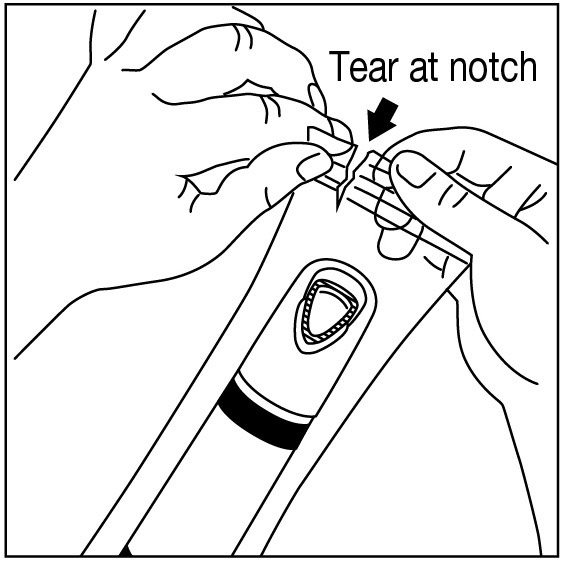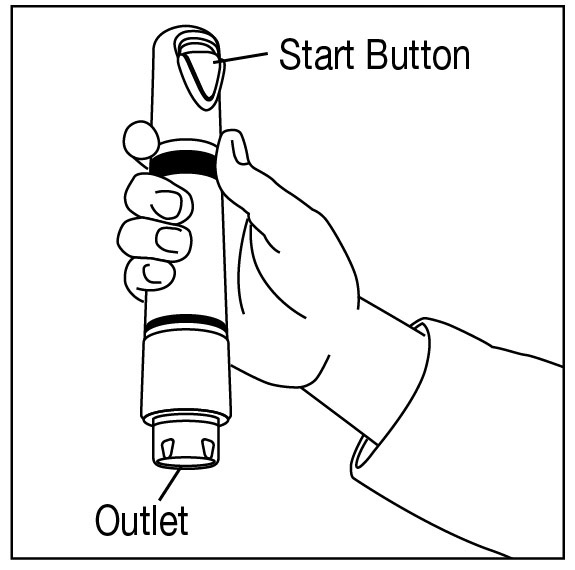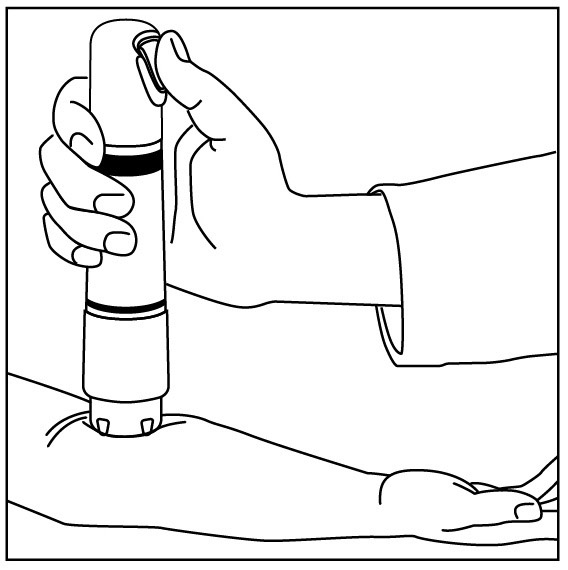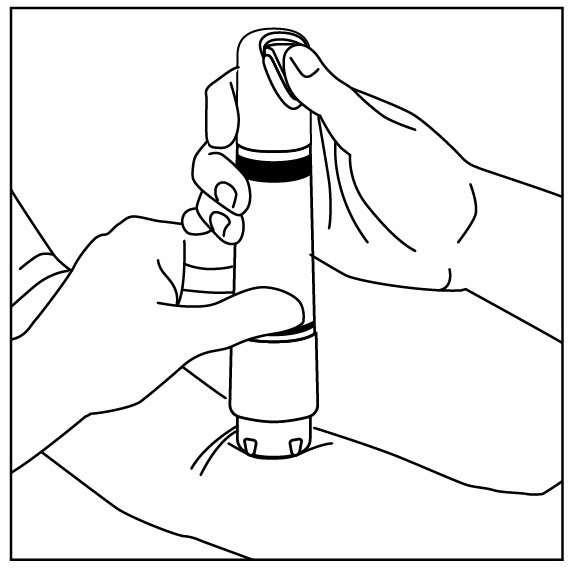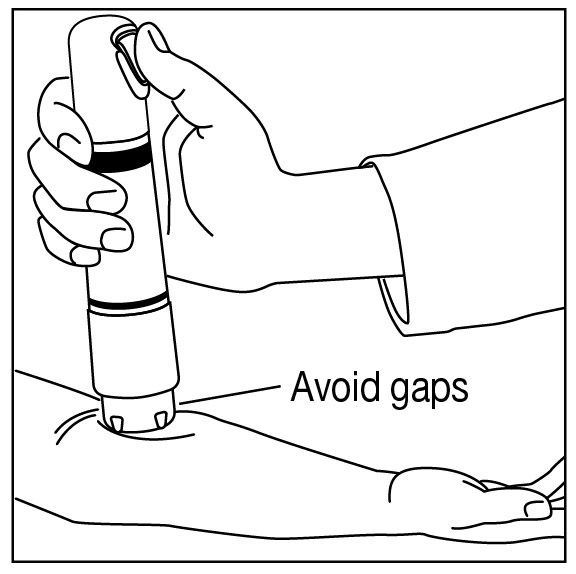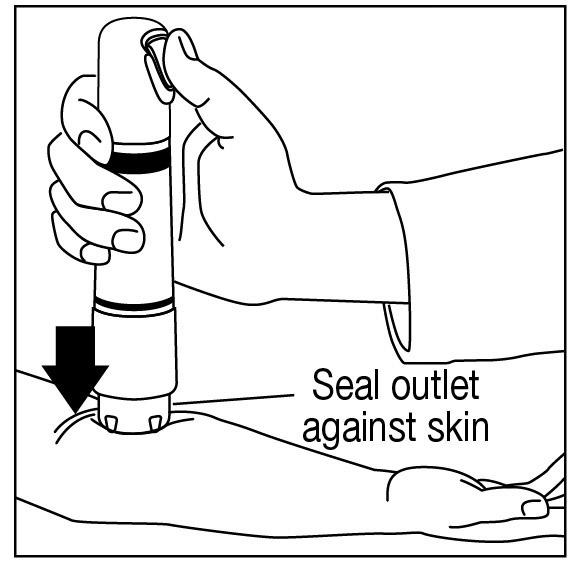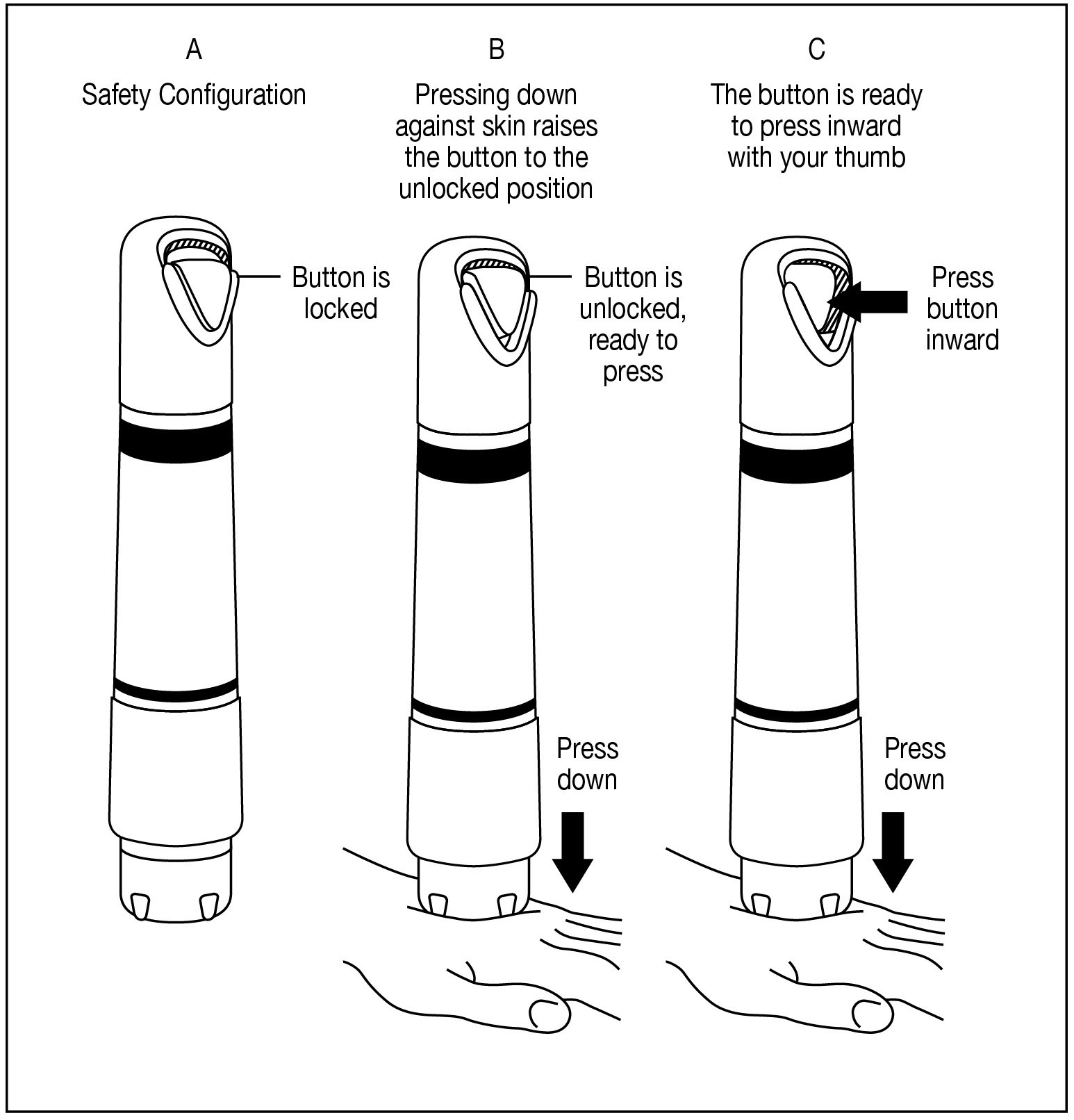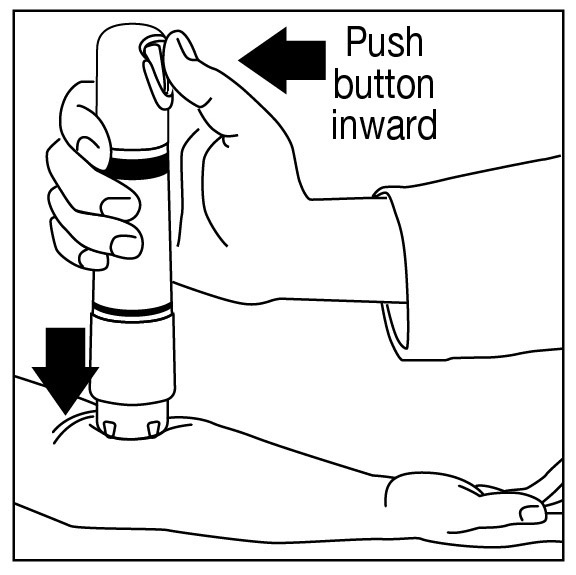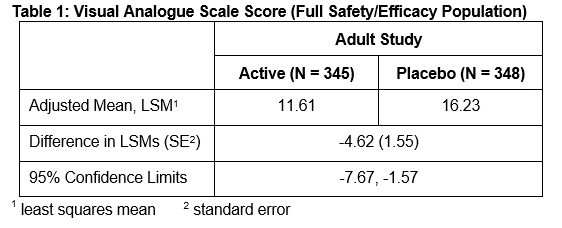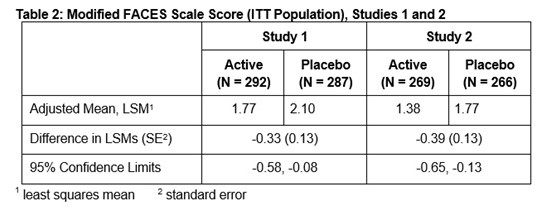 DRUG LABEL: Zingo
NDC: 61388-123 | Form: POWDER
Manufacturer: Powder Pharmaceutical Incorporated
Category: prescription | Type: HUMAN PRESCRIPTION DRUG LABEL
Date: 20251110

ACTIVE INGREDIENTS: LIDOCAINE HYDROCHLORIDE 0.5 mg/1 1

HIGHLIGHTS OF PRESCRIBING INFORMATION

These highlights do not include all the information needed to use ZINGO safely and effectively. See full prescribing information for ZINGO.

ZINGO (lidocaine hydrochloride monohydrate)

powder intradermal injection system

Initial U.S. Approval: 1948

------------------ RECENT MAJOR CHANGES-------------------

Warnings and Precautions, Methemoglobinemia (5.1) 11/2018

------------------INDICATIONS AND USAGE-------------------

- ZINGO is an amide local anesthetic indicated for use on intact skin to provide local analgesia prior to venipuncture or peripheral intravenous cannulation in children 3–18 years of age. (1)
- ZINGO is indicated for use on intact skin to provide topical local analgesia prior to venipuncture in adults. (1)

Important Limitations:

For use on intact skin only (1, 2)

For external use only (5)

---------------DOSAGE AND ADMINISTRATION---------------

- Apply one ZINGO (0.5 mg lidocaine hydrochloride monohydrate) to the site planned for venipuncture or intravenous cannulation, one to three minutes prior to needle insertion. (2.1)
- Perform the procedure within 10 minutes after ZINGO administration. (2)
- Use ZINGO only on intact skin. (2)

-------------DOSAGE FORMS AND STRENGTHS-------------

ZINGO is a sterile, single-use, powder intradermal injection system containing 0.5 mg lidocaine hydrochloride monohydrate. (3) ZINGO utilizes a helium-powered delivery system. (11)

---------------------CONTRAINDICATIONS---------------------

ZINGO is contraindicated in patients with a known history of sensitivity to local anesthetics of the amide type. (4)

---------------WARNINGS AND PRECAUTIONS---------------

- Methemoglobinemia: Cases of methemoglobinemia have been reported in association with local anesthetic use. (5.1)
- Use on intact skin only (2.1, 5)
- Avoid contact with the eye (2.1, 5)
- Do not use if device is dropped or the pouch is damaged or torn (2.1)
- Patients with bleeding tendencies or platelet disorders could have a higher risk of superficial dermal bleeding (5)

---------------------ADVERSE REACTIONS---------------------

The most common adverse reactions (>5%) are skin reactions at the site of administration: erythema, petechiae, edema, and pruritus (6.1)

To report SUSPECTED ADVERSE REACTIONS, contact 7T Pharma, LLC, at 1-800-941-2848 or FDA at 1-800-FDA-1088 or www.fda.gov/medwatch.

See 17 for PATIENT COUNSELING INFORMATION.

Revised: December 2025

FULL PRESCRIBING INFORMATION: CONTENTS*

1 INDICATIONS AND USAGE

2 DOSAGE AND ADMINISTRATION

2.1 Instructions for Use

3 DOSAGE FORMS AND STRENGTHS

4 CONTRAINDICATIONS

5 WARNINGS AND PRECAUTIONS

5.1 Methemoglobinemia

6 ADVERSE REACTIONS

6.1 Clinical Trials Experience

7 DRUG INTERACTIONS

8 USE IN SPECIFIC POPULATIONS

8.1 Pregnancy

8.2 Lactation

8.4 Pediatric Use

8.5 Geriatric Use

10 OVERDOSAGE

11 DESCRIPTION

12 CLINICAL PHARMACOLOGY

12.1 Mechanism of Action

12.2 Pharmacodynamics

12.3 Pharmacokinetics

13 NONCLINICAL TOXICOLOGY

13.1 Carcinogenesis, Mutagenesis, Impairment of Fertility

14 CLINICAL STUDIES

16 HOW SUPPLIED/STORAGE AND HANDLING

17 PATIENT COUNSELING INFORMATION

* Sections or subsections omitted from the full prescribing information are not listed.

1 INDICATIONS AND USAGE

ZINGO is indicated for use on intact skin to provide topical local analgesia prior to venipuncture or peripheral intravenous cannulation, in children 3–18 years of age.

ZINGO is indicated for use on intact skin to provide topical local analgesia prior to venipuncture in adults.

2 DOSAGE AND ADMINISTRATION

Apply one ZINGO (0.5 mg lidocaine hydrochloride monohydrate) to the site planned for venipuncture or intravenous cannulation, one to three minutes prior to needle insertion.

Perform the procedure within 10 minutes after ZINGO administration.

Use ZINGO only on intact skin.

Application of one additional ZINGO at a new location is acceptable after a failed attempt at venous access. Multiple administrations of ZINGO at the same location are not recommended.

When ZINGO is used concomitantly with other products containing local anesthetic agents, the amount absorbed from all sources should be considered, as local anesthetics are thought to have at least additive toxicities.

2.1 Instructions for Use

Prepare the Treatment Site and Device:

Examine the treatment site to ensure that the skin is intact. Clean the site, according to standard practice.

Visually inspect the pouch. Do not use if the pouch has been torn, or damaged or if the device has been dropped.

Tear open the pouch using the notch provided (Figure 1a). Remove ZINGO from the pouch, being careful not to touch the purple outlet (open end) to avoid contamination (Figure 1b).

Position ZINGO: Grip ZINGO and place on the application site, with one hand, as illustrated in Figure 2, or with both hands, as shown in Figure 3.

Ensure that the patient’s treatment site is supported to prevent movement. Seal the purple ZINGO outlet against the patient’s skin. Hold the device perpendicular to the skin, making sure that your thumb can reach the green start button.

Avoid gaps between the skin and the ZINGO outlet, like the one illustrated in Figure 4, as gaps will impede drug delivery.

Release the Safety Interlock: Apply adequate downward pressure to release the safety interlock, while maintaining the seal between ZINGO and the skin.

ZINGO is ready for administration when the green start button has moved into the upward position, as illustrated in Figure 5a.

ZINGO cannot be actuated without releasing the internal safety interlock, as illustrated in Figure 5b.

Administer ZINGO: While maintaining downward pressure, administer the dose by pressing the green start button, as illustrated in Figure 6. Do not move ZINGO during administration. Actuation is accompanied by a “popping” sound, indicating that the dose has been discharged.

Remove ZINGO: Remove ZINGO from the application site and dispose.

Begin Procedure: Start the venipuncture or intravenous cannulation procedure 1–3 minutes after ZINGO administration.

3 DOSAGE FORMS AND STRENGTHS

ZINGO (lidocaine hydrochloride monohydrate) powder intradermal injection system contains 0.5 mg of sterile lidocaine hydrochloride monohydrate.

4 CONTRAINDICATIONS

ZINGO is contraindicated in patients with a known history of sensitivity to local anesthetics of the amide type.

5 WARNINGS AND PRECAUTIONS

Do not use around the eyes.

Do not use ZINGO on body orifices, mucous membranes, or on areas with a compromised skin barrier. Only use ZINGO on skin locations where an adequate seal can be maintained.

Patients with severe hepatic disease or pseudocholinesterase deficiency, because of their inability to metabolize local anesthetics normally, are at a greater risk of developing toxic plasma concentrations of lidocaine.

Patients with bleeding tendencies or platelet disorders could have a higher risk of superficial dermal bleeding.

5.1 Methemoglobinemia

Cases of methemoglobinemia have been reported in association with local anesthetic use. Although all patients are at risk for methemoglobinemia, patients with glucose-6-phosphate dehydrogenase deficiency, congenital or idiopathic methemoglobinemia, cardiac or pulmonary compromise, infants under 6 months of age, and concurrent exposure to oxidizing agents or their metabolites are more susceptible to developing clinical manifestations of the condition. If local anesthetics must be used in these patients, close monitoring for symptoms and signs of methemoglobinemia is recommended.

Signs of methemoglobinemia may occur immediately or may be delayed some hours after exposure, and are characterized by a cyanotic skin discoloration and/or abnormal coloration of the blood. Methemoglobin levels may continue to rise; therefore, immediate treatment is required to avert more serious central nervous system and cardiovascular adverse effects, including seizures, coma, arrhythmias, and death. Discontinue ZINGO and any other oxidizing agents. Depending on the severity of the signs and symptoms, patients may respond to supportive care, i.e., oxygen therapy, hydration. A more severe clinical presentation may require treatment with methylene blue, exchange transfusion, or hyperbaric oxygen.

6 ADVERSE REACTIONS

6.1 Clinical Trials Experience

Because clinical trials are conducted under widely varying conditions, adverse reaction rates observed in the clinical trials of a
drug cannot be directly compared to rates in the clinical trials of another drug and may not reflect the rates observed in clinical
practice.
The safety of ZINGO has been evaluated in 10 clinical trials, five in adults and five in pediatric patients.
The five adult clinical trials consisted of a randomized, double-blind, parallel-arm, sham-placebo controlled Phase 3 trial that enrolled 693 patients, two randomized, double-blind, crossover design, sham-placebo controlled Phase 1 trials that enrolled 455 patients, and two open-label studies that enrolled 44 patients. A total of 742 adults received an active treatment with an active treatment that delivered a 0.5 mg dose of lidocaine, while 775 received placebo.
The five pediatric clinical trials consisted of five randomized, double-blind, parallel-arm, sham-placebo controlled trials in which 1761 patients, ages 3 to 18, received either ZINGO or a sham placebo device. A total of 906 pediatric patients received active treatment, while 855 received placebo.
Application Site Reaction
The application site was specifically assessed for four categories of skin site reaction (erythema, edema, pruritus, and petechiae).
In adults, erythema occurred in 67.3% of ZINGO-treated patients, and in 25.0% of placebo-treated patients. Petechiae occurred in 46.4% of ZINGO-treated patients, and in 7.0% of placebo-treated patients. Edema occurred in 4.3% of ZINGOtreated patients, and in 0.8% of placebo-treated patients. Pruritus occurred in 9.4% of ZINGO-treated patients and in 6.2% of placebo-treated patients.
In pediatric patients, erythema occurred in 53% of ZINGO-treated patients, and in 27% of placebo-treated patients. Petechiae occurred in 44% of ZINGO-treated patients, and in 5% of placebo-treated patients. Edema occurred in 8% of ZINGO-treated patients, and in 3% of placebo-treated patients. Pruritus occurred in 1% of patients in both treatment groups.
Adverse Reactions
Amongst the 742 adult patients receiving active treatment and 775 adult patients receiving sham placebo treatment in the 5 adult studies, the percentage of adult patients with any adverse reactions was 3.9% in the active-treated patients and 4.9% in the sham placebo treated patients.
Most adverse reactions were application-site related (i.e., hypoaesthesia (0% active, 0.5% sham placebo), burning (0.54% active, 0.4% sham placebo), and venipuncture site hemorrhage (0.4% active, 1.7% sham placebo)).
The most common systemic adverse reaction was dizziness, which occurred in 0.9% of active-treated adult patients and in 0.7% of sham placebo treated adult patients. No other systemic adverse events occurred in more than two patients in either treatment group.
Amongst the 906 pediatric patients receiving active treatment and 855 pediatric patients receiving sham placebo treatment, the percentage of pediatric patients with any adverse reactions was approximately 9% in each treatment group.
Most adverse reactions were application-site related (i.e., bruising, burning, pain, contusion, hemorrhage), occurring in 4% of pediatric patients in each treatment group.
The most common systemic adverse reactions were nausea (2%) and vomiting (1%).

7 DRUG INTERACTIONS

Patients who are administered local anesthetics are at increased risk of developing methemoglobinemia when concurrently exposed to the following drugs, which could include other local anesthetics:

Examples of Drugs Associated with Methemoglobinemia:

Class | Examples
Nitrates/Nitrites | nitric oxide, nitroglycerin, nitroprusside, nitrous oxide
Local anesthetics | articaine, benzocaine, bupivacaine, lidocaine, mepivacaine, prilocaine,; procaine, ropivacaine, tetracaine
Antineoplastic agents | cyclophosphamide, flutamide,; hydroxyurea, ifosfamide, rasburicase
Antibiotics | dapsone, nitrofurantoin, para-aminosalicylic acid, sulfonamides
Antimalarials | chloroquine, primaquine
Anticonvulsants | phenobarbital, phenytoin, sodium valproate,
Other drugs | acetaminophen, metoclopramide, quinine, sulfasalazine

8 USE IN SPECIFIC POPULATIONS

8.1 Pregnancy

Risk Summary
Available published data and decades of clinical use with lidocaine in pregnant women have not identified any drug-associated
risk for major birth defects, miscarriage, or other adverse maternal or fetal outcomes. Lidocaine is not detectable systemically following intradermal administration [see Clinical Pharmacology (12.3)], and maternal use is not expected to result in fetal exposure to the drug. Lidocaine has been previously tested for reproductive toxicity in animal studies. The following ratios are based on the assumption that the applied dose is completely absorbed through the skin.
In an animal reproduction study, pregnant rats administered lidocaine, containing 1:100,000 epinephrine, injected into the masseter muscle of the jaw or into the gum of the lower jaw at a dose of 6 mg/kg at 120-fold the single dermal administration (SDA) of 0.5 mg lidocaine on Gestation Day 11 resulted in developmental delays in neonatal behavior among offspring. In another animal reproduction study, no developmental toxicities were observed in rats administered lidocaine by subcutaneous route at doses up to 1200-fold the SDA or in rabbits up to 600-fold the SDA (see Data).

The background risk of major birth defects and miscarriage for the indicated population is unknown. All pregnancies carry some risk of birth defects, loss, or other adverse outcomes. In the U.S. general population, the estimated background risk of major birth defects and miscarriage in clinically recognized pregnancies is 2% to 4% and 15% to 20%, respectively.

Data
Animal Data
Lidocaine was not teratogenic in rats given subcutaneous doses up to 60 mg/kg [360 mg/m2 or 1200-fold the single dermal administration (SDA) of 0.5 mg lidocaine in a 60 kg individual (0.3 mg/m2)] or in rabbits up to 15 mg/kg (180 mg/m2 or 600-fold the SDA) during the period of organogenesis. In a published study, lidocaine administered to pregnant rats by continuous subcutaneous infusion during the period of organogenesis at doses of 100, 250, and 500 mg/kg/day, did not produce any structural abnormalities, but did result in lower fetal weights at 500 mg/kg/day (3000 mg/m2 or 10,000-fold the SDA on a mg/m2 basis) in the absence of maternal toxicity. Lidocaine, containing 1:100,000 epinephrine, at a dose of 6 mg/kg (36 mg/m2 or 120-fold the SDA) injected into the masseter muscle of the jaw or into the gum of the lower jaw of Long-Evans hooded pregnant rats on Gestation Day 11 led to developmental delays in neonatal behavior among offspring. Developmental delays were observed for negative geotaxis, static righting reflex, visual discrimination response,sensitivity and response to thermal and electrical shock stimuli, and water maze acquisition. The developmental delays of the neonatal animals were transient with responses becoming comparable to untreated animals later in life. The clinical relevance of the animal data is uncertain.

8.2 Lactation

Risk Summary
Published data report the presence of lidocaine and its metabolites in human milk in low amounts following parenteral administration, along with poor oral bioavailability. There are no data on the effect of lidocaine on the breastfed infant or the effect on milk production. There are no detectable plasma concentrations of lidocaine after subdermal administration of ZINGO; therefore, breastfeeding is not expected to result in exposure of the child to lidocaine [see Clinical Pharmacology (12.3)]. The developmental and health benefits of breastfeeding should be considered along with the mother’s clinical need for ZINGO and any potential adverse effects on the breastfed child from ZINGO or from the underlying maternal condition.

8.4 Pediatric Use

Safety and effectiveness in pediatric patients below the age of 3 years have not been established.

8.5 Geriatric Use

Of the 693 patients evaluated in a Phase 3 randomized, double blind, sham-placebo-controlled trial in adults, 17% were of 65 and over. The safety and effectiveness of ZINGO in geriatric patients were similar to that of ZINGO in adults under 65 years of age.

10 OVERDOSAGE

In adults following a single administration of ZINGO the plasma levels of lidocaine were below the limit of detection (5 ng/mL). Signs of central nervous system (CNS) toxicity may start at plasma concentrations of lidocaine as low as 1000 ng/mL, and the risk of seizures generally increases with increasing plasma levels. Very high levels of lidocaine can cause respiratory arrest, coma, decreases in cardiac output, total peripheral resistance, and mean arterial pressure, ventricular arrhythmias, and cardiac arrest. The toxicity of coadministered local anesthetics is thought to be at least additive. In the absence of massive topical overdose or oral ingestion, other etiologies for the clinical effects or overdosage from other sources of lidocaine or other local anesthetics should be considered. The management of overdosage includes close monitoring, supportive care, and symptomatic treatment. Dialysis is of negligible value in the treatment of acute overdosage of lidocaine.

11 DESCRIPTION

ZINGO® (lidocaine hydrochloride monohydrate) powder intradermal injection system contains 0.5 mg of sterile lidocaine hydrochloride monohydrate.

The chemical name is 2-diethylamino-2',6'-acetoxylidide, monohydrochloride, monohydrate. The molecular formula is C14H22N2O · HCl · H2O with a molecular weight of 288.8 Da. Lidocaine hydrochloride monohydrate, a local anesthetic of the amide class, has the following structural formula:

Lidocaine hydrochloride monohydrate is freely soluble in water, soluble in alcohol and chloroform, insoluble in ether, and melts at around 74–79°C.

ZINGO is a ready-to-use, sterile, single-use, disposable, needle-free delivery system. ZINGO consists of the following components: a drug reservoir cassette filled with 0.5 mg lidocaine hydrochloride monohydrate as a powder with a nominal particle size of 40 µm, a pressurized helium gas cylinder, and a safety interlock. The safety interlock prevents inadvertent actuation of the device. Once ZINGO is pressed against the skin, the interlock is released, allowing the button to be depressed to actuate the device. A sound similar to that of a popping balloon is emitted at the time ZINGO is actuated.

12 CLINICAL PHARMACOLOGY

12.1 Mechanism of Action

ZINGO delivers lidocaine hydrochloride monohydrate into the dermis. Lidocaine is an amide-type local anesthetic agent that blocks sodium ion channels required for the initiation and conduction of neuronal impulses, resulting in local anesthesia.

12.2 Pharmacodynamics

ZINGO provides local dermal analgesia within 1–3 minutes of application. Analgesia diminishes within 10 minutes of treatment.

12.3 Pharmacokinetics

Absorption

A single dose of ZINGO in adults did not produce detectable plasma concentrations of lidocaine (limit of quantitation 5 ng/mL) in any subject tested (n = 38).

Application of ZINGO to broken or inflamed skin, or multiple ZINGO applications, could result in systemic plasma levels of lidocaine that could produce systemic toxicity.

Distribution

When lidocaine is administered intravenously to healthy volunteers, the steady-state volume of distribution is approximately 0.8 to 1.3 L/kg. At much higher plasma concentrations (1 to 4 mcg/mL of free base) than those found following application of ZINGO, the plasma protein binding of lidocaine is concentration dependent. Lidocaine crosses the placental and blood brain barriers, presumably by passive diffusion. CNS toxicity may typically be observed around 5000 ng/mL of lidocaine; however a small number of patients reportedly may show signs of toxicity at approximately 1000 ng/mL.

Metabolism

It is not known if lidocaine is metabolized in the skin. Lidocaine is metabolized rapidly by the liver to a number of metabolites including monoethylglycinexylidide (MEGX) and glycinexylidide (GX), both of which have pharmacologic activity similar to, but less potent than that of lidocaine. The major metabolic pathway of lidocaine, sequential N-deethylation to monoethylglycinexylidide (MEGX) and glycinexylidide (GX), is primarily mediated by CYP1A2 with a minor role of CYP3A4. The metabolite, 2,6-xylidine, has unknown pharmacologic activity. Following intravenous administration of lidocaine, MEGX and GX concentrations in serum range from 11% to 36% and from 5% to 11% of lidocaine concentrations, respectively. Serum concentrations of MEGX are about one-third the serum lidocaine concentrations.

Elimination

The half-life of lidocaine elimination from the plasma following intravenous administration is approximately 1.8 hours. Lidocaine and its metabolites are excreted by the kidneys. More than 98% of an absorbed dose of lidocaine can be recovered in the urine as metabolites or parent drug. Less than 10% of lidocaine is excreted unchanged in adults, and approximately 20% is excreted unchanged in neonates. The systemic clearance is approximately 8–10 mL/min/kg. During intravenous studies, the elimination half-life of lidocaine was statistically significantly longer in elderly patients (2.5 hours) than in younger patients (1.5 hours).

13 NONCLINICAL TOXICOLOGY

13.1 Carcinogenesis, Mutagenesis, Impairment of Fertility

Carcinogenesis

Long-term studies in animals have not been performed to evaluate the carcinogenic potential of lidocaine.

Mutagenesis

No mutagenic potential of lidocaine was demonstrated in the in vitro Ames Bacterial Reverse Mutation Assay, the in vitro chromosome aberration assay using Chinese hamster ovary cells, and the in vivo mouse micronucleus assay.

Impairment of Fertility

ZINGO was not formally evaluated for effects on fertility. Significant systemic exposure to lidocaine is not expected under recommended conditions of use of ZINGO, as lidocaine levels were below the limit of detection in human studies. Lidocaine has been previously tested in animal studies for effects on fertility, however. The following ratios are based on the assumption that the applied dose is completely absorbed through the skin.

Lidocaine did not affect fertility in female rats when given via continuous subcutaneous infusion via osmotic minipumps up to doses of 250 mg/kg/day [1500 mg/m^2 or 5000-fold higher than the SDA of 0.5 mg lidocaine in a 60 kg individual (0.3 mg/m^2)]. Although lidocaine treatment of male rats increased the copulatory interval and led to a dose-related decreased homogenization resistant sperm head count, daily sperm production, and spermatogenic efficiency, the treatment did not affect overall fertility in male rats when given subcutaneous doses up to 60 mg/kg (360 mg/m^2 or 1200-fold the SDA).

14 CLINICAL STUDIES

Efficacy in Adults

The efficacy of ZINGO in adults was evaluated in a randomized, double-blind, parallel-arm, sham-placebo controlled trial in which adult patients who required a venipuncture or peripheral venous cannulation received either ZINGO or a sham placebo device.

Patients were treated with ZINGO or a placebo device at the antecubital fossa or back of the hand, between one and three minutes prior to venipuncture or peripheral venous cannulation. Measurements of pain were made immediately following the procedure. Efficacy was measured using a continuous 100 mm visual analogue scale ranging from 0 (“no pain”) to 100 (“worst possible pain”).

Many of the patients had chronic medical problems such as depression, hypertension, hypothyroidism, and hyperlipidemia and over one fourth of the population may have been at higher than average risk of dermal bleeding due to use of concomitant medications such as NSAIDs, aspirin, and corticosteroids.

Treatment with active drug resulted in less pain compared with placebo (see Table 1).

However, efficacy was primarily seen in patients undergoing venipuncture at the antecubital fossa, while patients undergoing cannulation at the back of the hand did not demonstrate a difference between active and sham administrations.

Efficacy in Pediatric Patients

The efficacy of ZINGO in patients 3–18 years of age was evaluated in two randomized, double-blind, parallel-arm, sham-placebo controlled trials in which pediatric patients received either ZINGO or a sham placebo device.

The overall patient population consisted of healthy pediatric patients as well as those with acute and chronic medical conditions (i.e., diabetes, asthma, seizure disorder, juvenile rheumatoid arthritis and renal or hepatic transplantation) ages 3–18 years. All patients required peripheral venipuncture or intravenous cannulation as part of their clinical care.

Two efficacy trials (Studies 1 and 2) were conducted during which patients were treated with ZINGO or a placebo device at the back of hand or antecubital fossa, between one and three minutes prior to venipuncture or peripheral venous cannulation. Measurements of pain were made immediately following the venous procedure. Efficacy was measured using a modified version of the Wong-Baker FACES pain rating scale [a categorical 6-point scale containing 6 faces ranging from 0 (“no hurt”) to 5 (“hurts worst”)].

In both studies, treatment with active drug resulted in less pain, from venipuncture or peripheral IV cannulation, compared with placebo (See Table 2).

16 HOW SUPPLIED/STORAGE AND HANDLING

NDC 61388-123 ZINGO® (lidocaine hydrochloride monohydrate) powder intradermal injection system contains 0.5 mg of sterile lidocaine hydrochloride monohydrate. ZINGO® is a single-dose device packaged in an individual clear pouch. Twelve pouched devices are placed in labeled cartons.

Cartons are stored at 20° to 25°C (68° to 77°F); excursions permitted between 15° to 30°C (59° to 86°F) [See USP Controlled Room Temperature].

17 PATIENT COUNSELING INFORMATION

Inform patients that use of local anesthetics may cause methemoglobinemia, a serious condition that must be treated promptly. Advise patients or caregivers to seek immediate medical attention if they or someone in their care experience the following signs or symptoms: pale, gray, or blue colored skin (cyanosis); headache; rapid heart rate; shortness of breath; lightheadedness; or fatigue.

Patients should be made aware that a sound similar to that of a popping balloon is emitted at the time ZINGO is actuated.

Patients should be informed that skin reactions including erythema, petechiae, pruritus and edema may occur.

Manufactured by:

Powder Pharmaceuticals, Inc.

Hong Kong, China

500113 Rev 03

ZINGO® is a trademark of Powder Pharmaceuticals, Incorporated.

OUTER PACKAGING and PRINCIPAL DISPLAY PANEL

Device Label

NDC 61388-123-26
ZINGO®
(lidocaine hydrochloride monohydrate)
powder intradermal injection system 0.5 mg
contains 1 sterile unit
Rx Only

Carton Label

NDC 61388-123-12
ZINGO®
(lidocaine hydrochloride monohydrate)
powder intradermal injection system 0.5 mg
contains 12 sterile units
Rx Only